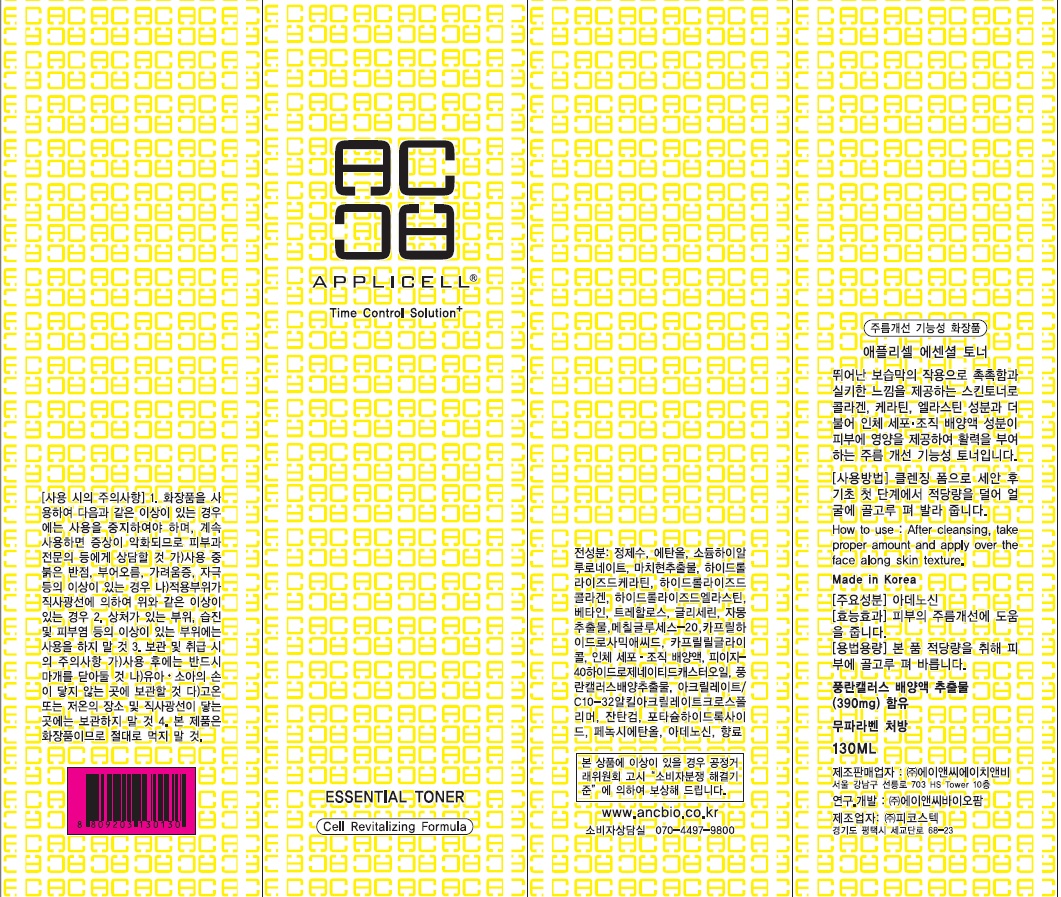 DRUG LABEL: Applicell Essential Toner
NDC: 71098-020 | Form: LIQUID
Manufacturer: Anc HnB Inc.
Category: otc | Type: HUMAN OTC DRUG LABEL
Date: 20161125

ACTIVE INGREDIENTS: Adenosine 0.05 g/130 mL
INACTIVE INGREDIENTS: Water; Alcohol

ACTIVE INGREDIENT

Active Ingredient: Adenosine 0.04%

INACTIVE INGREDIENT

Inactive Ingredients: Water, Alcohol, Sodium Hyaluronate, Portulaca Oleracea Extract, Hydrolyzed Keratin, Hydrolyzed Collagen, Hydrolyzed Elastin, Betaine, Trehalose, Citrus Paradisi (Grapefruit) Fruit Extract, Methyl Gluceth-20, Caprylhydroxamic Acid, Caprylyl Glycol, Human fibroblast Conditioned Media, PEG-40 Hydrogenated Castor Oil, Neofinetia Falcata Callus Culture Extract, Acrylates/C10-30 Alkyl Acrylate Crosspolymer, Xanthan Gum, Potassium Hydroxide, Phenoxyethanol, Fragrance

PURPOSE

Purpose: Skin Protectant

WARNINGS

Warnings: For external use only When using this product do not get into eyes, Stop use and ask a doctor if rash occurs Do not use on - deep puncture wounds - animal bites - serious burns Keep out of reach of children

KEEP OUT OF REACH OF CHILDREN

INDICATIONS & USAGE

Indications & usage: APPLICELL Essential Toner is the wrinkle functional toner that provides moisture, a silky feel and nourishment to the skin.

DOSAGE & ADMINISTRATION

How to use: After cleansing, take proper amount and apply over the face along skin texture.